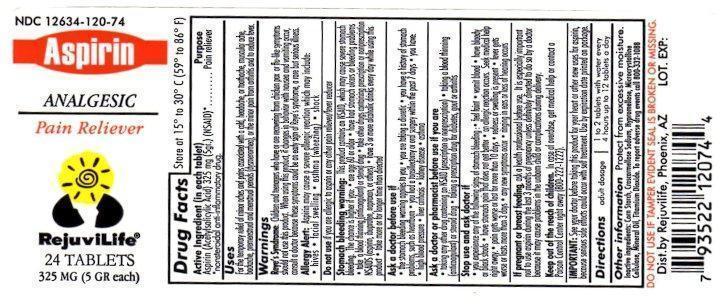 DRUG LABEL: Aspirin
NDC: 12634-120 | Form: TABLET
Manufacturer: Apotheca, Inc
Category: otc | Type: HUMAN OTC DRUG LABEL
Date: 20131011

ACTIVE INGREDIENTS: ASPIRIN 325 g/1 1
INACTIVE INGREDIENTS: STARCH, CORN; CROSCARMELLOSE SODIUM; HYPROMELLOSES; CELLULOSE, MICROCRYSTALLINE; MINERAL OIL; TITANIUM DIOXIDE

ASPIRIN TABLETS USP, 325 MG

ACTIVE INGREDIENT

Each tablet contains Aspirin 325 mg
Aspirin (Acetysalicylic Acid) 325 mg (5gr.) (NSAID)*

PURPOSE

Pain Reliever

Uses:

For the temporary relief of minor aches and pains due to:

headache, colds, muscle pain, menstrual pain, toothache, minor pain of arthritis or as directed by your doctor.

KEEP OUT OF REACH OF CHILDREN

Keep out of the reach of children. In case of overdose, get medical help or contact a Poison Control Center right away.

USES

Provides temporary relief of

- headache
- pain and fever of colds
- muscle pain
- toothache
- menstrual pain
- minor pain of arthritis.

WARNINGS

Reye’s syndrome: Children and teenagers who have or are recovering from chicken pox or flu-like symptoms should not use this product. When using this product, if changes in behavior with nausea and vomiting occur, consult a doctor because these symptoms could be an early sign of Reye’s syndrome, a rare but serious illness.Allergy alert: Aspirin may cause a severe allergic reaction, which may include, hives, facial swelling, shock, asthma (wheezing)

Stomach bleeding warning:This product contains an NSAID which may cause severe stomach bleeding. The chance is higher if you are age 60 or older, have had stomach ulcers or bleeding problems, take a blood thinning (anticoagulant) or steroid drug, take other drugs containing prescription or nonprescription NSAIDs (aspirin, ibuprofen, naproxen, or others); have 3 or more alcoholic drinks every day while using this product, take more or for a longer time than directed.

DOSAGE & ADMINISTRATION

Drink a full glass of water with each dose

Adults and children 12 years and over: take 1 to 2 tablets every 4 hours while symptoms last

Do not take more than 12 tablets in 24 hours unless directed by a doctor.

Children under 12 years: consult a doctor

INACTIVE INGREDIENT

corn starch, croscarmellose sodium, Hypromellose, microcrystalline cellulose, mineral oil, titanium dioxide

PRINCIPAL DISPLAY PANEL

MANUFACTURED BY:

Time-Cap Labs, Inc

Farmingdale, NY 11735

Repackaged & Relabeled by:

Apotheca, Inc

Phoenix, AZ 85006

Repackaged & Relabeled for:

RejuviLife

Phoenix, AZ 85006

NDC 12634-120-74

ASPIRIN

ANALGESIC

PAIN RELIEVER

REJUVILIFE

24 TABLETS

325 MG (5 GR EACH)